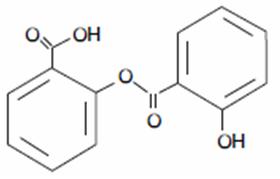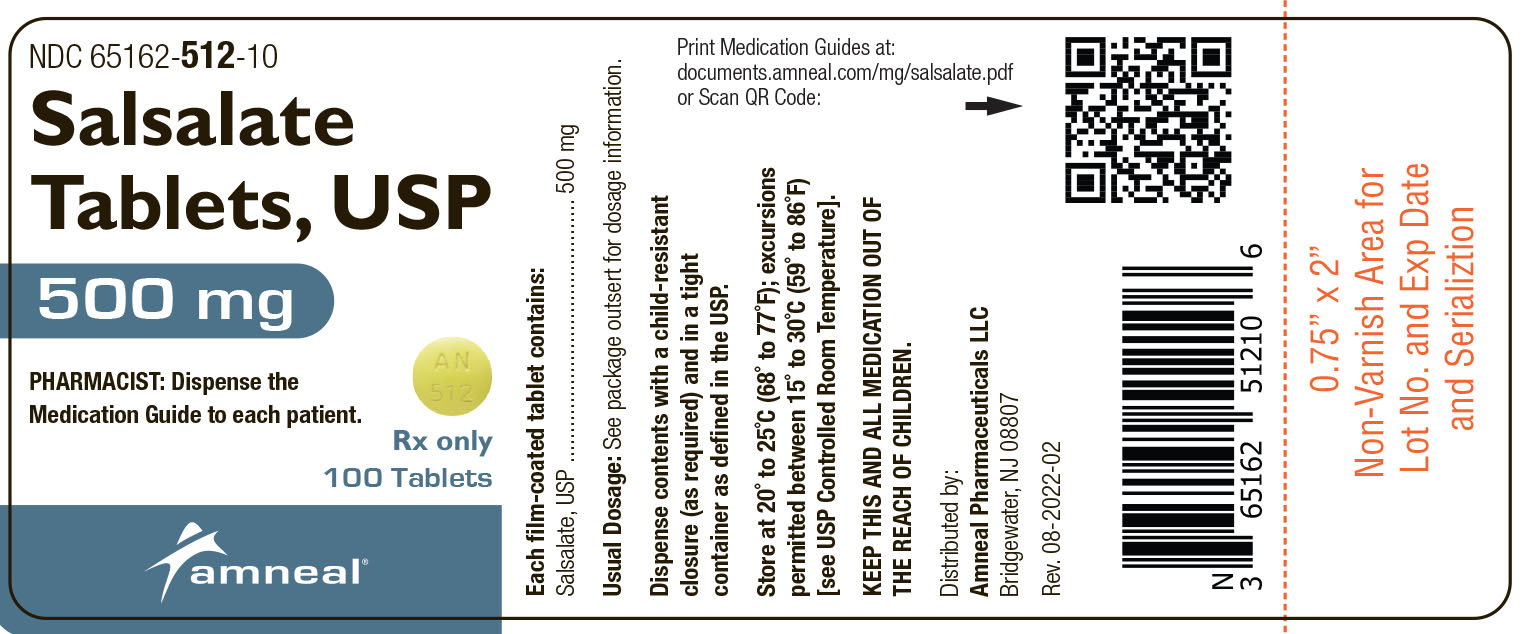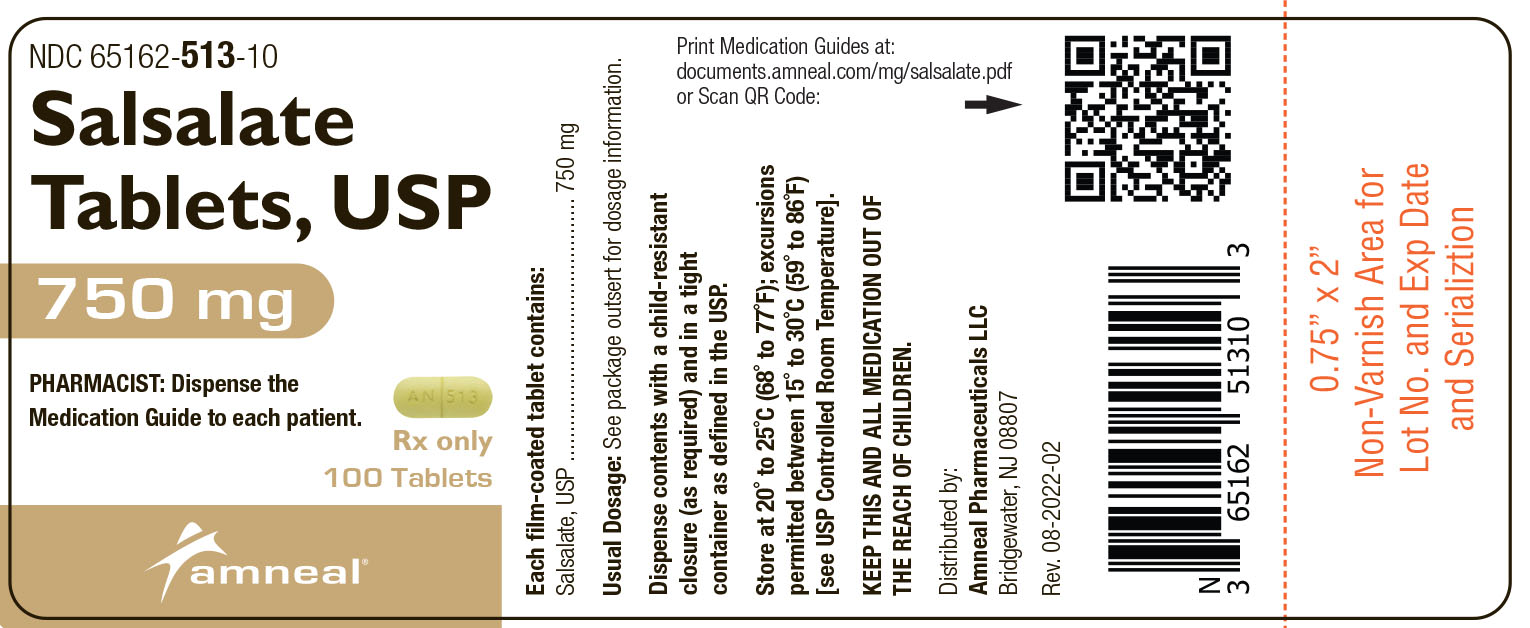 DRUG LABEL: Salsalate
NDC: 65162-512 | Form: TABLET
Manufacturer: Amneal Pharmaceuticals LLC
Category: prescription | Type: HUMAN PRESCRIPTION DRUG LABEL
Date: 20241030

ACTIVE INGREDIENTS: SALSALATE 500 mg/1 1
INACTIVE INGREDIENTS: CARNAUBA WAX; SILICON DIOXIDE; CROSCARMELLOSE SODIUM; D&C YELLOW NO. 10; HYPROMELLOSES; CELLULOSE, MICROCRYSTALLINE; POLYETHYLENE GLYCOL, UNSPECIFIED; STEARIC ACID; TITANIUM DIOXIDE

Salsalate Tablets, USP
500 mg and 750 mg
Rx Only

BOXED WARNING

Cardiovascular Risk

- NSAIDs may cause an increased risk of serious cardiovascular thrombotic events, myocardial infarction, and stroke, which can be fatal. This risk may increase with duration of use. Patients with cardiovascular disease or risk factors for cardiovascular disease may be at greater risk (see WARNINGS and CLINICAL TRIALS).
- Salsalate tablets are contraindicated for the treatment of perioperative pain in the setting of coronary artery bypass graft (CABG) surgery (see WARNINGS).

Gastrointestinal Risk

- NSAIDs cause an increased risk of serious gastrointestinal adverse events including bleeding, ulceration, and perforation of the stomach or intestines, which can be fatal. These events can occur at any time during use and without warning symptoms. Elderly patients are at greater risk for serious gastrointestinal events (see WARNINGS).

DESCRIPTION

Salsalate USP, is a nonsteroidal anti-inflammatory agent for oral administration. Chemically, salsalate, USP (salicylsalicylic acid or 2-hydroxy-benzoic acid, 2-carboxyphenyl ester) is a dimer of salicylic acid; its structural formula is shown below.

Chemical Structure:

Tablets:

Inactive Ingredients: Carnauba wax, Colloidal Silicon Dioxide, Croscarmellose

Sodium, D&C Yellow #10, Hypromellose, Microcrystalline Cellulose, Polyethylene Glycol, Stearic Acid, Titanium Dioxide,

CLINICAL PHARMACOLOGY

Salsalate is insoluble in acid gastric fluids (<0.1 mg/ml at pH 1.0), but readily soluble in the small intestine where it is partially hydrolyzed to two molecules of salicylic acid. A significant portion of the parent compound is absorbed unchanged and undergoes rapid esterase hydrolysis in the body: its half-life is about one hour. About 13% is excreted through the kidneys as a glucuronide conjugate of the parent compound, the remainder as salicylic acid and its metabolites. Thus, the amount of salicylic acid available from salsalate is about 15% less than from aspirin, when the two drugs are administered on a salicylic acid molar equivalent basis (3.6 g salsalate/5 g aspirin). Salicylic acid biotransformation is saturated at anti-inflammatory doses of salsalate. Such capacity-limited biotransformation results in an increase in the half-life of salicylic acid from 3.5 to 16 or more hours. Thus, dosing with salsalate twice a day will satisfactorily maintain blood levels within the desired therapeutic range (10 to 30 mg/100 ml) throughout the 12-hour intervals. Therapeutic blood levels continue for up to 16 hours after the last dose. The parent compound does not show capacity-limited biotransformation, nor does it accumulate in the plasma on multiple dosing. Food slows the absorption of all salicylates including salsalate.

The mode of anti-inflammatory action of salsalate and other nonsteroidal anti-inflammatory drugs is not fully defined. Although salicylic acid (the primary metabolite of salsalate) is a weak inhibitor of prostaglandin synthesis in vitro, salsalate appears to selectively inhibit prostaglandin synthesis in vivo^1, providing anti-inflammatory activity equivalent to aspirin^2 and indomethacin^3. Unlike aspirin, salsalate does not inhibit platelet aggregation^4. The usefulness of salicylic acid, the active in vivo product of salsalate, in the treatment of arthritic disorders has been established^5,6. In contrast to aspirin, salsalate causes no greater fecal gastrointestinal blood loss than placebo^7.

INDICATIONS AND USAGE

Carefully consider the potential benefits and risks of Salsalate tablets and other treatment options before deciding to use Salsalate tablets. Use the lowest effective dose for the shortest duration consistent with individual patient treatment goals (see WARNINGS). Salsalate is indicated for relief of the signs and symptoms of rheumatoid arthritis, osteoarthritis and related rheumatic disorder.

CONTRAINDICATIONS

Salsalate tablets are contraindicated in patients with known hypersensitivity to salsalate. Salsalate tablets should not be given to patients who have experienced asthma, urticaria, or allergic-type reactions after taking aspirin or other NSAIDs. Severe, rarely fatal, anaphylactic-like reactions to NSAIDs have been reported in such patients (see WARNINGS – Anaphylactoid Reactions, and PRECAUTIONS - Preexisting Asthma).

Salsalate tablets are contraindicated for the treatment of peri-operative pain in the setting of coronary artery bypass graft (CABG) surgery (see WARNINGS).

WARNINGS

Reye’s Syndrome may develop in individuals who have chicken pox, influenza, or flu symptoms. Some studies suggest a possible association between the development of Reye’s Syndrome and the use of medicines containing salicylate or aspirin. Salsalate contains a salicylate and therefore is not recommended for use in patients with chicken pox, influenza, or flu symptoms.

CARDIOVASCULAR EFFECTS

Cardiovascular Thrombotic Events

Clinical trials of several COX-2 selective and nonselective NSAIDs of up to three years duration have shown an increased risk of serious cardiovascular (CV) thrombotic events, myocardial infarction, and stroke, which can be fatal. All NSAIDs, both COX-2 selective and nonselective, may have a similar risk. Patients with known CV disease or risk factors for CV disease may be at greater risk. To minimize the potential risk for an adverse CV event in patients treated with an NSAID, the lowest effective dose should be used for the shortest duration possible. Physicians and patients should remain alert for the development of such events, even in the absence of previous CV symptoms. Patients should be informed about the signs and/or symptoms of serious CV events and the steps to take if they occur. There is no consistent evidence that concurrent use of aspirin mitigates the increased risk of serious CV thrombotic events associated with NSAID use. The concurrent use of aspirin and an NSAID does increase the risk of serious GI events (see GI WARNINGS).

Two large, controlled, clinical trials of a COX-2 selective NSAID for the treatment of pain in the first 10 to 14 days following CABG surgery found an increased incidence of myocardial infarction and stroke (see CONTRAINDICATIONS).

Hypertension

NSAIDs, including Salsalate tablets, can lead to onset of new hypertension or worsening of pre-existing hypertension, either of which may contribute to the increased incidence of CV events. Patients taking thiazides or loop diuretics may have impaired response to these therapies when taking NSAIDs. NSAIDs, including Salsalate tablets, should be used with caution in patients with hypertension. Blood pressure (BP) should be monitored closely during the initiation of NSAID treatment and throughout the course of therapy.

Congestive Heart Failure and Edema

Fluid retention and edema have been observed in some patients taking NSAIDs. Salsalate tablets should be used with caution in patients with fluid retention or heart failure.

Gastrointestinal Effects-Risk of Ulceration, Bleeding, and Perforation

NSAIDs, including Salsalate tablets, can cause serious gastrointestinal (GI) adverse events including inflammation, bleeding, ulceration, and perforation of the stomach, small intestine, or large intestine, which can be fatal. These serious adverse events can occur at any time, with or without warning symptoms, in patients treated with NSAIDs. Only one in five patients, who develop a serious upper GI adverse event on NSAID therapy, is symptomatic. Upper GI ulcers, gross bleeding, or perforation caused by NSAIDs occur in approximately 1% of patients treated for 3 to 6 months, and in about 2% to 4% of patients treated for one year. These trends continue with longer duration of use, increasing the likelihood of developing a serious GI event at some time during the course of therapy.

However, even short-term therapy is not without risk. NSAIDs should be prescribed with extreme caution in those with a prior history of ulcer disease or gastrointestinal bleeding. Patients with a prior history of peptic ulcer disease and/or gastrointestinal bleeding who use NSAIDs have a greater than 10-fold increased risk for developing a GI bleed compared to patients with neither of these risk factors. Other factors that increase the risk for GI bleeding in patients treated with NSAIDs include concomitant use of oral corticosteroids or anticoagulants, longer duration of NSAID therapy, smoking, use of alcohol, older age, and poor general health status. Most spontaneous reports of fatal GI events are in elderly or debilitated patients and therefore, special care should be taken in treating this population. To minimize the potential risk for an adverse GI event in patients treated with an NSAID, the lowest effective dose should be used for the shortest possible duration. Patients and physicians should remain alert for signs and symptoms of GI ulceration and bleeding during NSAID therapy and promptly initiate additional evaluation and treatment if a serious GI adverse event is suspected. This should include discontinuation of the NSAID until a serious GI adverse event is ruled out. For high risk patients, alternate therapies that do not involve NSAIDs should be considered.

Renal Effects

Long-term administration of NSAIDs has resulted in renal papillary necrosis and other renal injury. Renal toxicity has also been seen in patients in whom renal prostaglandins have a compensatory role in the maintenance of renal perfusion. In these patients, administration of a nonsteroidal anti-inflammatory drug may cause a dose-dependent reduction in prostaglandin formation and, secondarily, in renal blood flow, which may precipitate overt renal decompensation. Patients at greatest risk of this reaction are those with impaired renal function, heart failure, liver dysfunction, those taking diuretics and ACE inhibitors, and the elderly. Discontinuation of NSAID therapy is usually followed by recovery to the pretreatment state.

Advanced Renal Disease

No information is available from controlled clinical studies regarding the use of Salsalate tablets in patients with advanced renal disease. Therefore, treatment with Salsalate tablets are not recommended in these patients with advanced renal disease. If Salsalate tablets therapy must be initiated, close monitoring of the patient's renal function is advisable.

Anaphylactoid Reactions

Fetal Toxicity

Premature Closure of Fetal Ductus Arteriosus:

Avoid use of NSAIDs, including salsalate, in pregnant women at about 30 weeks gestation and later. NSAIDs, including salsalate, increase the risk of premature closure of the fetal ductus arteriosus at approximately this gestational age.

Oligohydramnios/Neonatal Renal Impairment:

Use of NSAIDs, including salsalate, at about 20 weeks gestation or later in pregnancy may cause fetal renal dysfunction leading to oligohydramnios and, in some cases, neonatal renal impairment. These adverse outcomes are seen, on average, after days to weeks of treatment, although oligohydramnios has been infrequently reported as soon as 48 hours after NSAID initiation. Oligohydramnios is often, but not always, reversible with treatment discontinuation. Complications of prolonged oligohydramnios may, for example, include limb contractures and delayed lung maturation. In some postmarketing cases of impaired neonatal renal function, invasive procedures such as exchange transfusion or dialysis were required.

If NSAID treatment is necessary between about 20 weeks and 30 weeks gestation, limit salsalate use to the lowest effective dose and shortest duration possible. Consider ultrasound monitoring of amniotic fluid if salsalate treatment extends beyond 48 hours. Discontinue salsalate if oligohydramnios occurs and follow up according to clinical practice (see PRECAUTIONS: Pregnancy).

Inform pregnant women to avoid use of salsalate and other NSAIDs starting at 30 weeks gestation because of the risk of the premature closing of the fetal ductus arteriosus. If treatment with salsalate is needed for a pregnant woman between about 20 to 30 weeks gestation, advise her that she may need to be monitored for oligohydramnios, if treatment continues for longer than 48 hours (see WARNINGS: Fetal Toxicity, PRECAUTIONS: Pregnancy).

PRECAUTIONS

General

Patients on treatment with salsalate should be warned not to take other salicylates so as to avoid potentially toxic concentrations. Great care should be exercised when salsalate is prescribed in the presence of chronic renal insufficiency or peptic ulcer disease. Protein binding of salicylic acid can be influenced by nutritional status, competitive binding of other drugs, and fluctuations in serum proteins caused by disease (rheumatoid arthritis, etc.).

Although cross reactivity, including bronchospasm, has been reported occasionally with non-acetylated salicylates, including salsalate, in aspirin-sensitive patients^8,9, salsalate is less likely than aspirin to induce asthma in such patients^10.

Salsalate tablets cannot be expected to substitute for corticosteroids or to treat corticosteroid insufficiency. Abrupt discontinuation of corticosteroids may lead to disease exacerbation. Patients on prolonged corticosteroid therapy should have their therapy tapered slowly if a decision is made to discontinue corticosteroids. The pharmacological activity of Salsalate tablets in reducing [fever and] inflammation may diminish the utility of these diagnostic signs in detecting complications of presumed noninfectious, painful conditions.

Hepatic Effects

Borderline elevations of one or more liver tests may occur in up to 15% of patients taking NSAIDs including Salsalate tablets. These laboratory abnormalities may progress, may remain unchanged, or may be transient with continuing therapy. Notable elevations of ALT or AST (approximately three or more times the upper limit of normal) have been reported in approximately 1% of patients in clinical trials with NSAIDs. In addition, rare cases of severe hepatic reactions, including jaundice and fatal fulminant hepatitis, liver necrosis and hepatic failure, some of them with fatal outcomes have been reported.

A patient with symptoms and/or signs suggesting liver dysfunction, or in whom an abnormal liver test has occurred, should be evaluated for evidence of the development of a more severe hepatic reaction while on therapy with Salsalate tablets. If clinical signs and symptoms consistent with liver disease develop, or if systemic manifestations occur (e.g., eosinophilia, rash, etc.), Salsalate tablets should be discontinued.

Hematological Effects

Anemia is sometimes seen in patients receiving NSAIDs, including Salsalate tablets. This may be due to fluid retention, occult or gross GI blood loss, or an incompletely described effect upon erythropoiesis. Patients on long-term treatment with NSAIDs, including Salsalate tablets, should have their hemoglobin or hematocrit checked if they exhibit any signs or symptoms of anemia. NSAIDs inhibit platelet aggregation and have been shown to prolong bleeding time in some patients. Unlike aspirin, their effect on platelet function is quantitatively less, of shorter duration, and reversible. Patients receiving Salsalate tablets, who may be adversely affected by alterations in platelet function, such as those with coagulation disorders or patients receiving anticoagulants, should be carefully monitored.

Preexisting Asthma

Patients with asthma may have aspirin-sensitive asthma. The use of aspirin in patients with aspirin-sensitive asthma has been associated with severe bronchospasm which can be fatal. Since cross reactivity, including bronchospasm, between aspirin and other nonsteroidal anti-inflammatory drugs has been reported in such aspirin-sensitive patients, Salsalate tablets should not be administered to patients with this form of aspirin sensitivity and should be used with caution in patients with preexisting asthma.

INFORMATION FOR PATIENTS

Patients should be informed of the following information before initiating therapy with an NSAID and periodically during the course of ongoing therapy. Patients should also be encouraged to read the NSAID Medication Guide that accompanies each prescription dispensed.

1. Salsalate tablets, like other NSAIDs, may cause serious CV side effects, such as MI or stroke, which may result in hospitalization and even death. Although serious CV events can occur without warning symptoms, patients should be alert for the signs and symptoms of chest pain, shortness of breath, weakness, slurring of speech, and should ask for medical advice when observing any indicative sign or symptoms. Patients should be apprised of the importance of this follow-up (see WARNINGS, Cardiovascular Effects).

2. Salsalate tablets, like other NSAIDs, can cause GI discomfort and, rarely, serious GI side effects, such as ulcers and bleeding, which may result in hospitalization and even death. Although serious GI tract ulcerations and bleeding can occur without warning symptoms, patients should be alert for the signs and symptoms of ulcerations and bleeding, and should ask for medical advice when observing any indicative sign or symptoms including epigastric pain, dyspepsia, melena, and hematemesis. Patients should be apprised of the importance of this follow-up (see WARNINGS, Gastrointestinal Effects: Risk of Ulceration, Bleeding, and Perforation).

3. Salsalate tablets like other NSAIDs, can cause serious skin side effects such as exfoliative dermatitis, SJS, and TEN, which may result in hospitalizations and even death. Although serious skin reactions may occur without warning, patients should be alert for the signs and symptoms of skin rash and blisters, fever, or other signs of hypersensitivity such as itching, and should ask for medical advice when observing any indicative signs or symptoms. Patients should be advised to stop the drug immediately if they develop any type of rash and contact their physicians as soon as possible.

4. Patients should promptly report signs or symptoms of unexplained weight gain or edema to their physicians.

5. Patients should be informed of the warning signs and symptoms of hepatotoxicity (e.g., nausea, fatigue, lethargy, pruritus, jaundice, right upper quadrant tenderness, and "flu-like" symptoms). If these occur, patients should be instructed to stop therapy and seek immediate medical therapy.

6. Patients should be informed of the signs of an anaphylactoid reaction (e.g. difficulty breathing, swelling of the face or throat). If these occur, patients should be instructed to seek immediate emergency help (see WARNINGS).

7. In late pregnancy, as with other NSAIDs, Salsalate tablets should be avoided because it will cause premature closure of the ductus arteriosus.

LABORATORY TESTS

Plasma salicylic acid concentrations should be periodically monitored during long-term treatment with salsalate to aid maintenance of therapeutically effective levels: 10 to 30 mg/100 ml. Toxic manifestations are not usually seen until plasma concentrations exceed 30 mg/100 ml (see OVERDOSAGE). Urinary pH should also be regularly monitored: sudden acidification, as from pH 6.5 to 5.5, can double the plasma level, resulting in toxicity.

Because serious GI tract ulcerations and bleeding can occur without warning symptoms, physicians should monitor for signs or symptoms of GI bleeding. Patients on long-term treatment with NSAIDs, should have their CBC and a chemistry profile checked periodically. If clinical signs and symptoms consistent with liver or renal disease develop, systemic manifestations occur (e.g., eosinophilia, rash, etc.) or if abnormal liver tests persist or worsen, Salsalate tablets should be discontinued.

DRUG INTERACTIONS

ACE-inhibitors

Reports suggest that NSAIDs may diminish the antihypertensive effect of ACE-inhibitors. This interaction should be given consideration in patients taking NSAIDs concomitantly with ACE-inhibitors.

Aspirin

Salicylates antagonize the uricosuric action of drugs used to treat gout. ASPIRIN AND OTHER SALICYLATE DRUGS WILL BE ADDITIVE TO SALSALATE AND MAY INCREASE PLASMA CONCENTRATIONS OF SALICYLIC ACID TO TOXIC LEVELS. Drugs and foods that raise urine pH will increase renal clearance and urinary excretion of salicylic acid, thus lowering plasma levels: acidifying drugs or foods will decrease urinary excretion and increase plasma levels. Salicylates given concomitantly with anticoagulant drugs may predispose to systemic bleeding. Salicylates may enhance the hypoglycemic effect of oral antidiabetic drugs of the sulfonylurea class. Salicylate competes with a number of drugs for protein binding sites, notably penicillin, thiopental, thyroxine, triiodothyronine, phenytoin, sulfinpyrazone, naproxen, warfarin, methotrexate, and possibly corticosteroids. [When Salsalate tablets are administered with aspirin, its protein binding is reduced, although the clearance of free Salsalate tablets are not altered. The clinical significance of this interaction is not known; however,] as with other NSAIDs, concomitant administration of salsalate and aspirin is not generally recommended because of the potential of increased adverse effects.

Furosemide

Clinical studies, as well as post marketing observations, have shown that Salsalate tablets can reduce the natriuretic effect-of furosemide and thiazides in some patients. This response has been attributed to inhibition of renal prostaglandin synthesis. During concomitant therapy with NSAIDs, the patient should be observed closely for signs of renal failure (see PRECAUTIONS, Renal Effects), as well as to assure diuretic efficacy.

Lithium

NSAIDs have produced an elevation of plasma lithium levels and a reduction in renal lithium clearance. The mean minimum lithium concentration increased 15% and the renal clearance was decreased by approximately 20%. These effects have been attributed to inhibition of renal prostaglandin synthesis by the NSAID. Thus, when NSAIDs and lithium are administered concurrently, subjects should be observed carefully for signs of lithium toxicity.

Methotrexate

NSAIDs have been reported to competitively inhibit methotrexate accumulation in rabbit kidney slices. This may indicate that they could enhance the toxicity of methotrexate. Caution should be used when NSAIDs are administered concomitantly with methotrexate.

Warfarin

The effcts of warfarin and NSAIDs on GI bleeding are synergistic, such that users of both drugs together have a risk of serious GI bleeding higher than users of either drug alone.

Drug/Laboratory Test Interactions: Salicylate competes with thyroid hormone for binding to plasma proteins, which may be reflected in a depressed plasma T4 value in some patients; thyroid function and basal metabolismare unaffected.

Carcinogenesis

No long-term animal studies have been performed with salsalate to evaluate its carcinogenic potential.

Pregnancy

Risk Summary

Use of NSAIDs, including salsalate, can cause premature closure of the fetal ductus arteriosus and fetal renal dysfunction leading to oligohydramnios and, in some cases, neonatal renal impairment. Because of these risks, limit dose and duration of salsalate use between about 20 and 30 weeks of gestation, and avoid salsalate use at about 30 weeks of gestation and later in pregnancy (see Clinical Considerations, Data).

Premature Closure of Fetal Ductus Arteriosus

Use of NSAIDs, including salsalate, at about 30 weeks gestation or later in pregnancy increases the risk of premature closure of the fetal ductus arteriosus.

Oligohydramnios/Neonatal Renal Impairment

Use of NSAIDs at about 20 weeks gestation or later in pregnancy has been associated with cases of fetal renal dysfunction leading to oligohydramnios, and in some cases, neonatal renal impairment.

Data from observational studies regarding other potential embryofetal risks of NSAID use in women in the first or second trimesters of pregnancy are inconclusive. In the general U.S. population, all clinically recognized pregnancies, regardless of drug exposure, have a background rate of 2% to 4% for major malformations, and 15% to 20% for pregnancy loss. Reproductive studies conducted in rats and rabbits have not demonstrated evidence of developmental abnormalities. However, animal reproduction studies are not always predictive of human response. There are no adequate and well-controlled studies in pregnant women. Based on animal data, prostaglandins have been shown to have an important role in endometrial vascular permeability, blastocyst implantation, and decidualization. In animal studies, administration of prostaglandin synthesis inhibitors such as [active moiety], resulted in increased pre- and post-implantation loss. Prostaglandins also have been shown to have an important role in fetal kidney development. In published animal studies, prostaglandin synthesis inhibitors have been reported to impair kidney development when administered at clinically relevant doses.

Clinical Considerations

Fetal/Neonatal Adverse Reactions

Premature Closure of Fetal Ductus Arteriosus:

Avoid use of NSAIDs in women at about 30 weeks gestation and later in pregnancy, because NSAIDs, including salsalate, can cause premature closure of the fetal ductus arteriosus (see Data).

Oligohydramnios/Neonatal Renal Impairment

If an NSAID is necessary at about 20 weeks gestation or later in pregnancy, limit the use to the lowest effective dose and shortest duration possible. If salsalate treatment extends beyond 48 hours, consider monitoring with ultrasound for oligohydramnios. If oligohydramnios occurs, discontinue salsalate and follow up according to clinical practice (see Data).

Data

Human Data

Premature Closure of Fetal Ductus Arteriosus:

Published literature reports that the use of NSAIDs at about 30 weeks of gestation and later in pregnancy may cause premature closure of the fetal ductus arteriosus.

Oligohydramnios/Neonatal Renal Impairment:

Published studies and postmarketing reports describe maternal NSAID use at about 20 weeks gestation or later in pregnancy associated with fetal renal dysfunction leading to oligohydramnios, and in some cases, neonatal renal impairment. These adverse outcomes are seen, on average, after days to weeks of treatment, although oligohydramnios has been infrequently reported as soon as 48 hours after NSAID initiation. In many cases, but not all, the decrease in amniotic fluid was transient and reversible with cessation of the drug. There have been a limited number of case reports of maternal NSAID use and neonatal renal dysfunction without oligohydramnios, some of which were irreversible. Some cases of neonatal renal dysfunction required treatment with invasive procedures, such as exchange transfusion or dialysis.

Methodological limitations of these postmarketing studies and reports include lack of a control group; limited information regarding dose, duration, and timing of drug exposure; and concomitant use of other medications. These limitations preclude establishing a reliable estimate of the risk of adverse fetal and neonatal outcomes with maternal NSAID use. Because the published safety data on neonatal outcomes involved mostly preterm infants, the generalizability of certain reported risks to the full-term infant exposed to NSAIDs through maternal use is uncertain.

Labor and Delivery

There exist no adequate and well-controlled studies in pregnant women. Although adverse effects on mother or infant have not been reported with salsalate use during labor, caution is advised when anti-inflammatory dosage is involved. However, other salicylates have been associated with prolonged gestation and labor, maternal and neonatal bleeding sequelae, potentiation of narcotic and barbiturate effects (respiratory or cardiac arrest in the mother), delivery problems and stillbirth. In rat studies with NSAIDs, as with other drugs known to inhibit prostaglandin synthesis, an increased incidence of dystocia, delayed parturition, and decreased pup survival occurred. The effects of Salsalate tablets on labor and delivery in pregnant women are unknown.

Nursing Mothers

It is not known whether salsalate per se is excreted in human milk; salicylic acid, the primary metabolite of salsalate, has been shown to appear in human milk in concentrations approximating the maternal blood level. Thus, the infant of a mother on salsalate therapy might ingest in mother’s milk 30 to 80% as much salicylate per kg body weight as the mother is taking. Accordingly, caution should be exercised when salsalate is administered to a nursing woman.

Pediatric Use

Safety and effectiveness of salsalate use in children have not been established (see WARNINGS section).

Geriatric Use

As with any NSAIDs, caution should be exercised in treating the elderly (65 years and older).

ADVERSE REACTIONS

In two well-controlled clinical trials, the following reversible adverse experiences characteristic of salicylates were most commonly reported with salsalate (n-280 pts; listed in descending order of frequency): tinnitus, nausea, hearing impairment, rash, and vertigo. These common symptoms of salicylates, i.e., tinnitus or reversible hearing impairment, are often used as a guide to therapy.

Although cause-and-effect relationships have not been established, spontaneous reports over a ten-year period have included the following additional medically significant adverse experiences: abdominal pain, abnormal hepatic function, anaphylactic shock, angioedema, bronchospasm, decreased creatinine clearance, diarrhea, G.I. bleeding, hepatitis, hypotension, nephritis and urticaria.

To report SUSPECTED ADVERSE REACTIONS, contact Amneal Pharmaceuticals at 1-877-835-5472 or FDA at 1-800-FDA-1088 or www.fda.gov/medwatch.

Drug abuse and dependence have not been reported with salsalate.

OVERDOSAGE

Death has followed ingestion of 10 to 30 g of salicylates in adults, but much larger amounts have been ingested without fatal outcome.

Symptoms: The usual symptoms of salicylism - tinnitus, vertigo, headache, confusion, drowsiness, sweating, hyperventilation, vomiting and diarrhea - will occur. More severe intoxication will lead to disruption of electrolyte balance and blood pH, and hyperthermia and dehydration.

Treatment: Further absorption of salsalate from the G.I. tract should be prevented by emesis (syrup of ipecac), and, if necessary, by gastric lavage.

Fluid and electrolyte imbalance should be corrected by the administration of appropriate I.V. therapy. Adequate renal function should be maintained. Hemodialysis or peritoneal dialysis may be required in extreme cases.

DOSAGE AND ADMINISTRATION

Carefully consider the potential benefits and risks of Salsalate tablets and other treatment options before deciding to use Salsalate tablets. Use the lowest effective dose for the shortest duration consistent with individual patient treatment goals (see WARNINGS).

After observing the response to initial therapy with Salsalate tablets, the dose and frequency should be adjusted to suit an individual patient's needs. Salsalate is indicated for relief of the signs and symptoms of rheumatoid arthritis, osteoarthritis and related rheumatic disorder.

Adults: The usual dosage is 3000 mg daily, given in divided doses as follows:

1) two doses of two 750 mg tablets; 2) two doses of three 500 mg tablets; or 3) three doses of two 500 mg tablets. Some patients, e.g., the elderly, may require a lower dosage to achieve therapeutic blood concentrations and to avoid the more common side effects such as auditory.

Alleviation of symptoms is gradual, and full benefit may not be evident for 3 to 4 days, when plasma salicylate levels have achieved steady-state. There is no evidence for development of tissue tolerance (tachyphylaxis), but salicylate therapy may induce increased activity of metabolizing liver enzymes, causing a greater rate of salicyluric acid production and excretion, with a resultant increase in dosage requirement for maintenance of therapeutic serum salicylate levels.

Children: Dosage recommendations and indications for salsalate use in children have not been established.

HOW SUPPLIED

Salsalate tablets, USP 500 mg are available as yellow colored, round, film-coated tablets debossed “AN” over “512” on one side and plain on the other.
They are supplied as follows:

Bottles of 100 NDC 65162-512-10
Bottles of 500 NDC 65162-512-50
Bottles of 1,000ct NDC 65162-512-11

Salsalate tablets, USP 750 mg are available as yellow colored, capsule-shaped, scored, film-coated tablets debossed “AN 513” on one side and plain on the other.
They are supplied as follows:

Bottles of100 NDC 65162-513-10
Bottles of 500 NDC 65162-513-50
Bottles of 1,000 NDC 65162-513-11

Dispense contents with a child-resistant closure (as required) and in a tight container as defined in the USP.

Store at 20°C to 25°C (68°F to 77°F); excursions permitted between 15° to 30°C (59° to 86°F) [see USP Controlled Room Temperature].

Rx only

REFERENCES

1. Morris HG, Sherman NA, McQuain C, et al: Effects of Salsalate (Non-

Acetylated Salicylate) and Aspirin (ASA) on Serum Prostaglandins in Humans. Ther. Drug Monit. 7:435-438, 1985.

2. April PA, Curran NJ, Ekohlm BP, et al: Multicenter Comparative Study of Salsalate (SSA) vs Aspirin (ASA) in Rheumatoid Arthritis (RA), Arthritis Rheumatism 30 (4 supplement):S93, 1987.

3. Deodhar SD, McLeod MM, Dick WC, et al: A Short-Term Comparative Trial of Salsalate and Indomethacin in Rheumatoid Arthritis. Curr. Med. Res. Opin., 5:185-188, 1977.

4. Estes D, Kaplan K: Lack of Platelet Effect With the Aspirin Analog, Salsalate, Arthritis and Rheumatism, 23:1303-1307, 1980.

5. Dick C, Dick PH, Nuki G, et al: Effect of Anti-inflammatory Drug Therapy on Clearance of 133Xe from Knee Joints of Patients with Rheumatoid Arthritis. British Med. J. 3:278-280, 1969.

6. Dick WC, Grayson MF, Woodburn A, et al: Indices of Inflammatory Activity. Ann. of the Rheum. Dis. 29:643-648, 1970.

7. Cohen A:Fecal Blood Loss and Plasma Salicylate Study of Salicylsalicylic Acid and Aspirin. J. Clin. Pharmacol. 19:242-247, 1979.

8. Chudwin DS, Strub M. Golden HE, et al: Sensitivity to Non-Acetylated Salicylates in a Patient with Asthma, Nasal Polyps, and Rheumatoid Arthritis. Annals of Allergy 57:133-134, 1986.

9. Spector SL, Wangaard CH, Farr RS: Aspirin and Concomitant Idiosyncrasies in Adult Asthmatic Patients. J. Allergy Clin. Immunol 64:500-506, 1979.

10. Stevenson DD, Schrank PJ, Hougham AJ, et al: Salsalate Cross Sensitivity in Aspirin-Sensitive Asthmatics. J. Allergy Clin. Immunol 81:181, 1988.

Distributed by:
Amneal Pharmaceuticals LLC
Bridgewater, NJ 08807

Rev. 08-2022-02

Dispense with Medication Guide available at: documents.amneal.com/mg/salsalate.pdf

Medication Guide for Nonsteroidal Anti-inflammatory Drugs (NSAIDs)

Dispense with Medication Guide available at: documents.amneal.com/mg/salsalate.pdf

What is the most important information I should know about medicines called Nonsteroidal Anti-inflammatory Drugs (NSAIDs)?

NSAIDs can cause serious side effects, including:

- Increased risk of a heart attack or stroke that can lead to death. This risk may happen early in treatment and may increase:

- with increasing doses of NSAIDs
- with longer use of NSAIDs

Do not take NSAIDs right before or after a heart surgery called a “coronary artery bypass graft (CABG).”

Avoid taking NSAIDs after a recent heart attack, unless your healthcare provider tells you to. You may have an increased risk of another heart attack if you take NSAIDs after a recent heart attack.

- Increased risk of bleeding, ulcers, and tears (perforation) of the esophagus (tube leading from the mouth to the stomach), stomach and intestines:

- anytime during use
- without warning symptoms
- that may cause death

The risk of getting an ulcer or bleeding increases with:

- past history of stomach ulcers, or stomach or intestinal bleeding with use of NSAIDs
- taking medicines called “corticosteroids”, “anticoagulants”, “SSRIs”, or “SNRIs”
- increasing doses of NSAIDs
- longer use of NSAIDs
- smoking
- drinking alcohol
- oolder age
- poor health
- advanced liver disease
- bleeding problems

NSAIDs should only be used:

- exactly as prescribed
- at the lowest dose possible for your treatment
- for the shortest time needed

What are NSAIDs?
NSAIDs are used to treat pain and redness, swelling, and heat (inflammation) from medical conditions such as different types of arthritis, menstrual cramps, and other types of short-term pain.

Who should not take NSAIDs?
Do not take NSAIDS:

- if you have had an asthma attack, hives, or other allergic reaction with aspirin or any other NSAIDs.
- right before or after heart bypass surgery.

Before taking NSAIDs, tell your health care provider about all of your medical conditions, including if you:

- have liver or kidney problems
- have high blood pressure
- have asthma
- are pregnant or plan to become pregnant. Taking NSAIDs at about 20 weeks of pregnancy or later may harm your unborn baby. If you need to take NSAIDs for more than 2 days when you are between 20 and 30 weeks of pregnancy, your healthcare provider may need to monitor the amount of fluid in your womb around your baby. You should not take NSAIDs after about 30 weeks of pregnancy.
- are breastfeeding or plan to breast feed.

Tell your health care provider about all of the medicines you take, including prescription or over-the-counter medicines, vitamins or herbal supplements. NSAIDs and some other medicines can interact with each other and cause serious side effects. Do not start taking new medicine without talking to your health care provider first.

What are the possible side effects of NSAIDs?
NSAIDs can cause serious side effects, including:
See “What is the most important information I should know about medicines called Nonsteroidal Anti-inflammatory Drugs (NSAIDs)?”

- ·new or worse high blood pressure
- heart failure
- liver problems including liver failure
- kidney problems including kidney failure
- low red blood cells (anemia)
- life-threatening skin reactions
- life-threatening allergic reactions
- Other side effects of NSAIDs include: stomach pain, constipation, diarrhea, gas, heartburn, nausea, vomiting and dizziness.

Get emergency help right away if you get any of the following symptoms:

- shortness of breath or trouble breathing
- chest pain
- weakness in one part or side of your body
- slurred speech
- swelling of the face or throat

Stop taking your NSAID and call your health care provider right away if you get any of the following symptoms:

- ·nausea
- more tired or weaker than usual
- diarrhea
- itching
- your skin or eyes look yellow
- indigestion or stomach pain
- flu-like symptoms
- ·vomit blood
- there is blood in your bowel movement or it is black and sticky like tar
- unusual weight gain
- skin rash or blisters with fever
- swelling of the arms, legs, hands, and feet

If you take too much of your NSAID, call your health care provider or get medical help right away.
These are not all the possible side effects of NSAIDs. For more information, ask your health care provider or pharmacist about NSAIDs.
Call your doctor for medical advice about side effects. You may report side effects to FDA at 1-800-FDA-1088.

Other information about NSAIDs

- Aspirin is an NSAID but it does not increase the chance of a heart attack. Aspirin can cause bleeding in the brain, stomach, and intestines. Aspirin can also cause ulcers in the stomach and intestines.
- Some NSAIDs are sold in lower doses without a prescription (over-the-counter). Talk to your health care provider before using over-the-counter NSAIDs for more than 10 days.

General information about the safe and effective use of NSAIDs
Medicines are sometimes prescribed for purposes other than those listed in a Medication Guide. Do not use NSAIDs for a condition for which it was not prescribed. Do not give NSAIDs to other people, even if they have the same symptoms that you have. It may harm them.
If you would like more information about NSAIDs, talk with your health care provider. You can ask your pharmacist or health care provider for information about NSAIDs that is written for health professionals.

Distributed by:
Amneal Pharmaceuticals LLC

Bridgewater, NJ 08807
For more information, go to www.amneal.com or call 1-877-835-5472.

This Medication Guide has been approved by the U.S. Food and Drug Administration. Revised: 08-2022-00